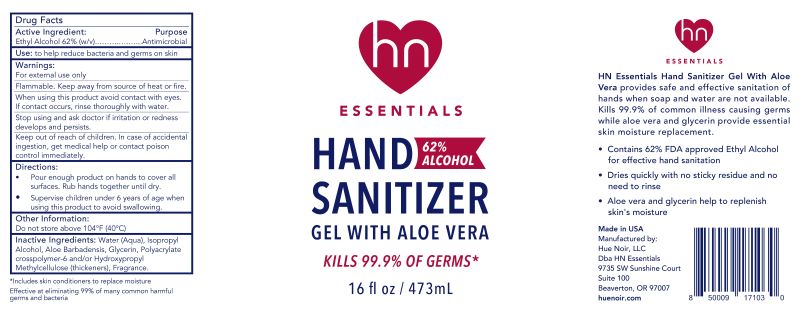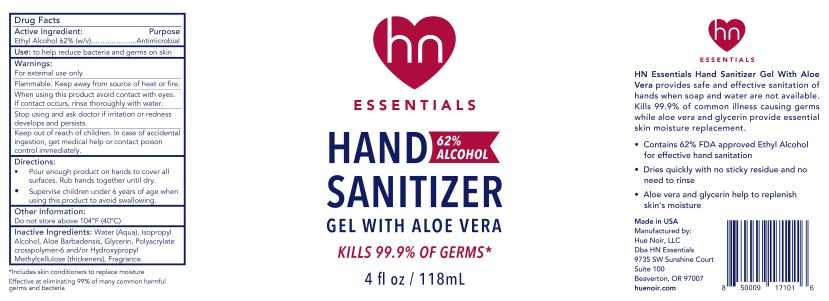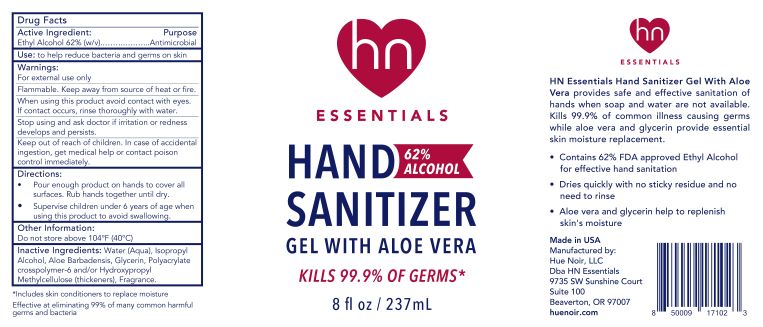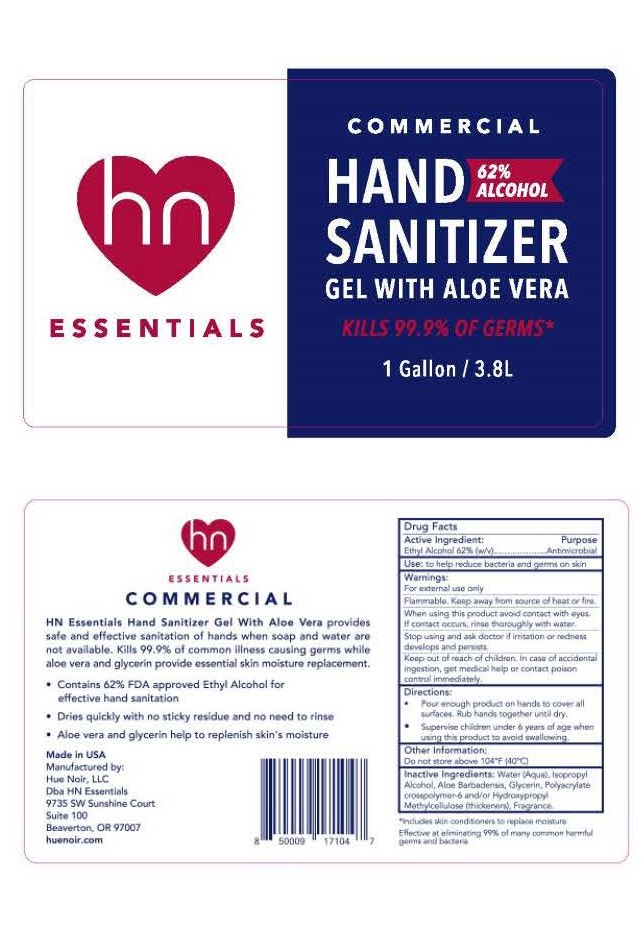 DRUG LABEL: HN Essentials Hand Sanitizer Gel with Aloe Vera
NDC: 80920-855 | Form: SOLUTION
Manufacturer: Hue Noir, LLC
Category: otc | Type: HUMAN OTC DRUG LABEL
Date: 20211222

ACTIVE INGREDIENTS: ALCOHOL 65 mL/100 mL
INACTIVE INGREDIENTS: GLYCERIN 2 mL/100 mL; ALOE 2 mL/100 mL; ISOPROPYL ALCOHOL 1 mL/100 mL; WATER 29.15 mL/100 mL; FRAGRANCE CLEAN ORC0600327 .05 mL/100 mL; HYDROXYPROPYL CELLULOSE (110000 WAMW) .40 mL/100 mL; ACRYLATES CROSSPOLYMER-6 0.40 mL/100 mL

Active ingredient:

Active ingredient: Ethyl Alcohol 62% (v/v)

Purpose

Purpose: Antimicrobial

Use

Use: to help reduce bacteria and germs on skin

Warnings:

For external use only

Flammable. Keep away from source of heat or fire.

When using this product avoid contact with eyes.

If contact occurs, rinse thoroughly with water.

STOP USE

Stop using and ask doctor if irritation or redness develops and persists.

Keep out of reach of children. In case of accidental ingestion, get medical help or contact poison control immediately.

Directions:

- Pour enough product on hands to conver all surfaces. Rub hands together until dry.
- Supervise children under 6 years of age when using this product to avoid swallowing.

Other Information:

Do not store above 104°F (40°C)

Inactive Ingredients:

Water (Aqua), Isopropyl Alcohol, Aloe Barbadensis, Glycerin, Polyacrylate crosspolymer-6 and/or Hydroxypropyl Methylcellulos (thickeners), Fragrance.

Package Label - Principal Display Panel NDC: 80920-855-04

HN Essentials

Hand Sanitizer Gel with Aloe Vera

62% Alcohol

Kills 99.9% of Germs*

4 fl oz/ 118 mL

Package Label - Principal Display Panel NDC: 80920-855-08

HN Essentials

Hand Sanitizer Gel with Aloe Vera

62% Alcohol

Kills 99.9% of Germs*

8 fl oz/ 237 mL

Package Label - Principal Display Panel NDC: 80920-855-16

HN Essentials

Hand Sanitizer Gel with Aloe Vera

62% Alcohol

Kills 99.9% of Germs*

16 fl oz/ 473 mL

Package Label - Principal Display Panel NDC: 80920-855-10

HN Essentials

Hand Sanitizer Gel with Aloe Vera

62% Alcohol

Kills 99.9% of Germs*

1gal/ 3.8 mL